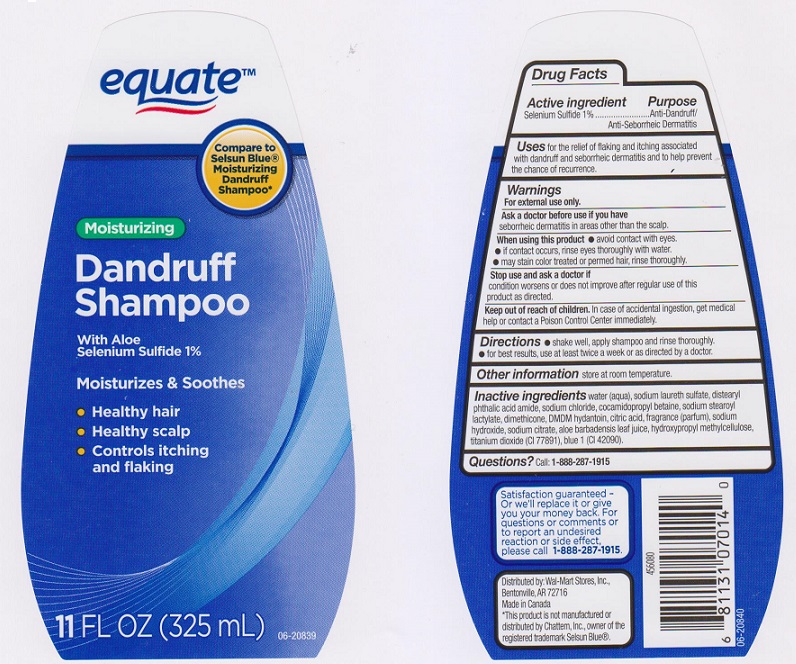 DRUG LABEL: EQUATE
NDC: 49035-522 | Form: LIQUID
Manufacturer: WAL-MART STORES INC
Category: otc | Type: HUMAN OTC DRUG LABEL
Date: 20151124

ACTIVE INGREDIENTS: SELENIUM SULFIDE 10 mg/1 mL
INACTIVE INGREDIENTS: WATER; SODIUM LAURETH SULFATE; DISTEARYL PHTHALAMIC ACID; SODIUM CHLORIDE; COCAMIDOPROPYL BETAINE; SODIUM STEAROYL LACTYLATE; DIMETHICONE; DMDM HYDANTOIN; CITRIC ACID MONOHYDRATE; SODIUM HYDROXIDE; SODIUM CITRATE; ALOE VERA LEAF; HYPROMELLOSES; TITANIUM DIOXIDE; FD&C BLUE NO. 1

DRUG FACTS

Active ingredient

Selenium Sulfide 1%

Purpose

Anti-Dandruff/Anti-Seborrheic Dermatitis

Uses

For the relief of flaking and itching associated with dandruff and seborrheic dermatitis and to help prevent the chance of recurrence.

Warnings

For external use only.

Ask a doctor if you have

seborrheic dermatitis in areas other than the scalp.

When using this product

- Avoid contact with eyes
- if contact occurs, rinse eyes thoroughly with water
- may stain color treated or permed hair, rinse thoroughly

Stop use and ask a doctor if

condition worsens or does not improve after regular use of this product as directed

Keep out of reach of children.

In case of accidental ingestion, get medical help or contact a Poison Control Center immediately.

Directions

- shake well, apply shampoo and rinse thoroughly
- for best results, use at least twice a week or as directed by a doctor

Other information

store at room temperature

Inactive ingredients

Water (Aqua), Sodium Laureth Sulfate, Distearyl Phthalic Acid Amide, Sodium Chloride, Cocamidopropyl Betaine, Sodium Stearoyl Lactylate, Dimethicone, DMDM Hydantoin, Citric Acid, Fragrance (Parfum), Sodium Hydroxide, Sodium Citrate, Aloe Barbadensis Leaf Juice, Hydroxypropyl Methylcellulose, Titanium Dioxide (CI 77891), Blue 1 (CI 42090).

Questions?

Call: 1-888-287-1915